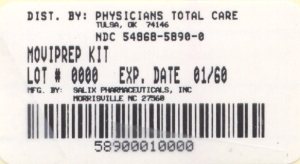 DRUG LABEL: MOVIPREP
NDC: 54868-5890 | Form: KIT | Route: ORAL
Manufacturer: Physicians Total Care, Inc.
Category: prescription | Type: HUMAN PRESCRIPTION DRUG LABEL
Date: 20091130

ACTIVE INGREDIENTS: POLYETHYLENE GLYCOL 3350 100 g/1 L; SODIUM SULFATE 7.5 g/1 L; SODIUM CHLORIDE 2.69 g/1 L; POTASSIUM CHLORIDE 1.015 g/1 L; ASCORBIC ACID 4.7 g/1 L; SODIUM ASCORBATE 5.9 g/1 L
INACTIVE INGREDIENTS: ASPARTAME; LEMON; ACESULFAME POTASSIUM

1 INDICATIONS AND USAGE

MoviPrep® is indicated for cleansing of the colon as a preparation for colonoscopy in adults 18 years of age or older.

2 DOSAGE AND ADMINISTRATION

The MoviPrep dose for colon cleansing for adult patients is 2 liters (approximately 64 ounces) of MoviPrep solution (with 1 additional liter of clear fluids) taken orally prior to the colonoscopy in one of the following ways:

1. Split-dose MoviPrep regimen: The evening before the colonoscopy, take the first liter of MoviPrep solution over one hour (one 8 ounce glass every 15 minutes) and then drink 0.5 liters (approximately 16 ounces) of clear fluid. Then, on the morning of the colonoscopy, take the second liter of MoviPrep solution over one hour and then drink 0.5 liters of clear liquid at least one hour prior to the start of the colonoscopy; or
2. Evening only (Full-dose) MoviPrep regimen: Around 6 PM in the evening before the colonoscopy, take the first liter of MoviPrep solution over one hour (one 8 ounce glass every 15 minutes) and then about 1.5 hours later take the second liter of MoviPrep solution over one hour. In addition, take 1 liter (approximately 32 ounces) of additional clear liquid during the evening before the colonoscopy.

Preparation of the MoviPrep solution:

MoviPrep solution is prepared by emptying the contents of 1 pouch A and 1 pouch B into a suitable glass container (or the container provided) and adding to the container 1 liter of lukewarm water. Mix the solution to ensure that the ingredients are completely dissolved. If the patient prefers, the MoviPrep solution can be refrigerated prior to drinking. The reconstituted solution should be used within 24 hours.

After consumption of the first liter of MoviPrep solution, the above mixing procedure should be repeated with the second pouch A and pouch B to reconstitute the second liter of the MoviPrep solution.

3 DOSAGE FORMS AND STRENGTHS

MoviPrep is available in a carton that contains 4 separate pouches (2 of pouch A and 2 of pouch B). Each pouch A contains 100 grams of polyethylene glycol (PEG) 3350, NF, 7.5 grams of sodium sulfate, USP, 2.691 grams of sodium chloride, USP, and 1.015 grams of potassium chloride, USP, plus the following excipients: aspartame, NF (sweetener), acesulfame potassium, NF (sweetener), and lemon flavoring. Each pouch B contains 4.7 grams of ascorbic acid, USP and 5.9 grams of sodium ascorbate, USP.

4 CONTRAINDICATIONS

MoviPrep is contraindicated in patients who have had a severe hypersensitivity reaction to any of its components.

5 WARNINGS AND PRECAUTIONS

MoviPrep should be used with caution in patients with severe ulcerative colitis, ileus, gastrointestinal obstruction or perforation, gastric retention, toxic colitis, or toxic megacolon

General

Patients with impaired gag reflex and patients prone to regurgitation or aspiration should be observed during the administration of MoviPrep. If a patient experiences severe bloating, abdominal distention, or abdominal pain, administration should be slowed or temporarily discontinued until the symptoms abate. If gastrointestinal obstruction or perforation is suspected, appropriate tests should be performed to rule out these conditions before administration of MoviPrep®.

Phenylketonurics: MoviPrep contains phenylalanine – a maximum of 2.33 mg of phenylalanine per treatment.

No additional ingredients (e.g., flavorings) should be added to the MoviPrep solution.

Since MoviPrep contains sodium ascorbate and ascorbic acid, MoviPrep should be used with caution in patients with glucose-6-phosphate dehydrogenase (G-6-PD) deficiency especially G-6-PD deficiency patients with an active infection, with a history of hemolysis, or taking concomitant medications known to precipitate hemolytic reactions.

5.1 Seizures

There have been rare reports of generalized tonic-clonic seizures associated with use of polyethylene glycol colon preparation products in patients with no prior history of seizures. The seizure cases were associated with electrolyte abnormalities (e.g., hyponatremia, hypokalemia). The neurologic abnormalities resolved with correction of fluid and electrolyte abnormalities. Therefore, MoviPrep should be used with caution in patients using concomitant medications that increase the risk of electrolyte abnormalities [such as diuretics or angiotensin converting enzyme (ACE)-inhibitors] or in patients with known or suspected hyponatremia. Consider performing baseline and post-colonoscopy laboratory tests (sodium, potassium, calcium, creatinine, and BUN) in these patients.

6 ADVERSE REACTIONS

6.1 Clinical Studies Experience

In the MoviPrep trials, abdominal distension, anal discomfort, thirst, nausea, and abdominal pain were some of the most common adverse reactions to MoviPrep administration. Since diarrhea was considered as a part of the efficacy of MoviPrep, diarrhea was not defined as an adverse reaction in the clinical studies. Tables 1 and 2 display the most common drug-related adverse reactions of MoviPrep and its comparator in the controlled MoviPrep trials.

Table 1: The Most Common Drug-Related Adverse Reactions* (≥ 2%) in the Study of MoviPrep vs. 4 liter Polyethylene Glycol plus Electrolytes Solution
 | MoviPrep®; (split dose); N=180 | 4L PEG + E†; N=179
 | n (% = n/N) | n (% = n/N)
Malaise | 35 (19.4) | 32 (17.9)
Nausea | 26 (14.4) | 36 (20.1)
Abdominal pain | 24 (13.3) | 27 (15.1)
Vomiting | 14 (7.8) | 23 (12.8)
Upper abdominal pain | 10 (5.6) | 11 (6.1)
Dyspepsia | 5 (2.8) | 2 (1.1)

* Drug-related adverse reactions were adverse events that were possibly, probably, or definitely related to the study drug.
† 4L PEG + E is 4 liter Polyethylene Glycol plus Electrolytes Solution

Table 2: The Most Common Drug-Related Adverse Reactions* (≥ 5%) in the Study of MoviPrep vs. 90 mL Oral Sodium Phosphate Solution
 | MoviPrep® (evening-only) (full dose) N=169 | 90 mL OSPS† N=171
 | n (% = n/N) | n (% = n/N)
Abdominal distension | 101 (59.8) | 70 (40.9)
Anal discomfort | 87 (51.5) | 89 (52.0)
Thirst | 80 (47.3) | 112 (65.5)
Nausea | 80 (47.3) | 80 (46.8)
Abdominal paint | 66 (39.1) | 55 (32.2)
Sleep disorder | 59 (34.9) | 49 (28.7)
Rigors | 57 (33.7) | 51 (29.8)
Hunger | 51 (30.2) | 121 (70.8)
Malaise | 45 (26.6) | 90 (52.6)
Vomiting | 12 (7.1) | 14 (8.2)
Dizziness | 11 (6.5) | 31 (18.1)
Headache | 3 (1.8) | 9 (5.3)
Hypokalemia | 0 (0) | 10 (5.8)
Hyperphosphatemia | 0 (0) | 10 (5.8)

* Drug-related adverse reactions were adverse events that were possibly, probably, or definitely related to the study drug. In addition to the recording of spontaneous adverse events, patients were also specifically asked about the occurrence of the following symptoms: shivering, anal irritations, abdominal bloating or fullness, sleep loss, nausea, vomiting, weakness, hunger sensation, abdominal cramps or pain, thirst sensation, and dizziness.
† OSPS is Oral Sodium Phosphate Solution

Isolated cases of urticaria, rhinorrhea, dermatitis, and anaphylactic reaction have been reported with PEG-based products and may represent allergic reactions.

Published literature contains isolated reports of serious adverse events following the administration of PEG-based products in patients over 60 years of age. These adverse events included upper gastrointestinal bleeding from a Mallory-Weiss tear, esophageal perforation, asystole, and acute pulmonary edema after aspirating the PEG-based preparation.

6.2 Postmarketing Experience

In addition to adverse events reported from clinical trials, the following adverse events have been identified during post-approval use of MoviPrep. Because they are reported voluntarily from a population of unknown size, estimates of frequency cannot be made. These events have been chosen for inclusion due to either their seriousness, frequency of reporting or causal connection to MoviPrep, or a combination of these factors.

General: Hypersensitivity reactions including anaphylaxis, rash, urticaria, lip and facial swelling, dyspnea, chest tightness and throat tightness.

7 DRUG INTERACTIONS

Oral medication administered within 1 hour of the start of administration of MoviPrep may be flushed from the gastrointestinal tract and the medication may not be absorbed.

8 USE IN SPECIFIC POPULATIONS

8.1 Pregnancy: Teratogenic Effects

Pregnancy Category C. Animal reproduction studies have not been performed with MoviPrep. It is also not known if MoviPrep can cause fetal harm when administered to a pregnant woman or can affect reproductive capacity. MoviPrep should be given to a pregnant woman only if clearly needed.

8.3 Nursing Mothers

Because many drugs are excreted in human milk, caution should be exercised when MoviPrep is administered to a nursing woman.

8.4 Pediatric Use

The safety and effectiveness of MoviPrep in pediatric patients has not been established.

8.5 Geriatric Use

Of the 413 patients in clinical studies receiving MoviPrep, 91 (22%) patients were aged 65 or older, while 25 (6%) patients were over 75 years of age. No overall differences in safety or effectiveness were observed between geriatric patients and younger patients, and other reported clinical experience has not identified differences in responses between geriatric patients and younger patients, but greater sensitivity of some older individuals cannot be ruled out.

10 OVERDOSAGE

There have been no reported cases of overdose with MoviPrep. Purposeful or gross accidental ingestion of more than the recommended dose of MoviPrep might be expected to lead to severe electrolyte disturbances, including hyponatremia and/or hypokalemia, as well as dehydration and hypovolemia, with signs and symptoms of these disturbances. The patient who has taken an overdose should be monitored carefully, and treated symptomatically for complications until stable.

11 DESCRIPTION

MoviPrep® consists of 4 separate pouches (2 of pouch A and 2 of pouch B) containing white to yellow powder for reconstitution. Each pouch A contains 100 grams of polyethylene glycol (PEG) 3350, NF, 7.5 grams of sodium sulfate, USP, 2.691 grams of sodium chloride, USP, and 1.015 grams of potassium chloride, USP, plus the following excipients: aspartame, NF (sweetener), acesulfame potassium, NF (sweetener), and lemon flavoring. Each pouch B contains 4.7 grams of ascorbic acid, USP and 5.9 grams of sodium ascorbate, USP. When 1 pouch A and 1 pouch B are dissolved together in water to a volume of 1 liter, MoviPrep (PEG-3350, sodium sulfate, sodium chloride, potassium chloride, sodium ascorbate, and ascorbic acid) is an oral solution having a lemon taste.
The entire, reconstituted, 2-liter MoviPrep colon preparation contains 200 grams of PEG-3350, 15 grams of sodium sulfate, 5.38 grams of sodium chloride, 2.03 grams of potassium chloride, 9.4 grams of ascorbic acid, and 11.8 grams of sodium ascorbate plus the following excipients: aspartame (sweetener), acesulfame potassium (sweetener), and lemon flavoring.

12 CLINICAL PHARMACOLOGY

MoviPrep produces a watery stool leading to cleansing of the colon. The osmotic activity of polyethylene glycol 3350, sodium sulfate, sodium chloride, potassium chloride, sodium ascorbate, and ascorbic acid, when taken with 1 liter of additional clear fluid, usually results in no net absorption or excretion of ions or water.

The pharmacokinetics of MoviPrep have not been studied in patients with renal or hepatic insufficiency.

13 NONCLINICAL TOXICOLOGY

13.1 Carcinogenesis, Mutagenesis, Impairment of Fertility

Long-term studies in animals to evaluate the carcinogenic potential have not been performed with MoviPrep®. Studies to evaluate potential for impairment of fertility or mutagenic potential have not been performed with MoviPrep®.

14 CLINICAL STUDIES

The colon cleansing efficacy and safety of MoviPrep was evaluated in two randomized, actively-controlled, multi-center, investigator-blinded, phase 3 trials in patients scheduled to have an elective colonoscopy.

In the first study, patients were randomized to one of the following two colon preparation treatments: 1) 2 liters of MoviPrep with 1 additional liter of clear fluid split into two doses (during the evening before and the morning of the colonoscopy) and 2) 4 liters of polyethylene glycol plus electrolytes solution (4L PEG + E) split into two doses (during the evening before and the morning of the colonoscopy). Patients were allowed to have a morning breakfast, a light lunch, clear soup and/or plain yogurt for dinner. Dinner had to be completed at least one hour prior to initiation of the colon preparation administration.

The primary efficacy endpoint was the proportion of patients with effective colon cleansing as judged by blinded gastroenterologists on the basis of videotapes recorded during the colonoscopy.
The blinded gastroenterologists graded the colon cleansing twice (during introduction and withdrawal of the colonoscope) and the poorer of the two assessments was used in the primary efficacy analysis.

The efficacy analysis included 308 adult patients who had an elective colonoscopy. Patients ranged in age from 18 to 88 years old (mean age about 59 years old) with 52% female and 48% male patients. Table 3 displays the results.

Table 3: Effectiveness of Overall Colon Cleansing in the Study of MoviPrep vs 4 Liter Polyethylene Glycol plus Electrolytes Solution
 | Responders; A* or B† (%) | C‡ (%) | D§ (%)
MoviPrep®; (N=153) | 88.9 | 9.8 | 1.3
4L PEG + E¶; (N=155) | 94.8 | 4.5 | 0.6

* A: colon empty and clean or presence of clear liquid, but easily removed by suction
† B: brown liquid or semisolid remaining amounts of stool, fully removable by suction or displaceable, thus allowing a complete visualization of the gut mucosa
‡ C: semisolid amounts of stool, only partially removable with a risk of incomplete visualization of the gut mucosa
§ D: semisolid or solid amounts of stool; consequently colonoscopy incomplete or needed to be terminated. 4 L PEG+E's responder rate was not significantly higher than MoviPrep's responder rate.
¶ 4L PEG + E is 4 Liter Polyethylene Glycol plus Electrolytes Solution

In the second study, patients were randomized to one of the following two colon preparation treatments: 1) 2 liters of MoviPrep with 1 additional liter of clear fluid in the evening prior to the colonoscopy and 2) 90 mL of oral sodium phosphate solution (90 mL OSPS) with at least 2 liters of additional clear fluid during the day and evening prior to the colonoscopy. Patients randomized to MoviPrep therapy were allowed to have a morning breakfast; a light lunch; and clear soup and/or plain yogurt for dinner. Dinner had to be completed at least one hour prior to initiation of the colon preparation administration.
The primary efficacy endpoint was the proportion of patients with effective colon cleansing as judged by the colonoscopist and one blinded gastroenterologist (on the basis of videotapes recorded during the colonoscopy). In case of a discrepancy between the colonoscopist and the blinded gastroenterologist, a second blinded gastroenterologist made the final efficacy determination.

The efficacy analysis included 280 adult patients who had an elective colonoscopy. Patients ranged in age from 21 to 76 years old (mean age about 53 years old) with 47% female and 53% male patients. Table 4 displays the results.

Table 4: Effectiveness of Overall Colon Cleansing in the Study of MoviPrep vs 90mL Oral Sodium Phosphate Solution
 | Responders; A* or B† (%) | C‡ (%) | D§ (%)
MoviPrep®; (N=137) | 73.0 | 23.4 | 3.6
90 mL OSPS¶; (N=143) | 64.4 | 29.4 | 6.3

* A: empty and clean or clear liquid (transparent, yellow, or green)
† B: brown liquid or semisolid remaining small amounts of stool, fully removable by suction or displaceable allowing a complete visualization of the underlying mucosa
‡ C: semi solid only partially removable/displaceable stools; risk of incomplete examination of the underlying mucosa
§ D: heavy and hard stool making the segment examination uninterpretable and, consequently, the colonoscopy needed to be terminated
¶
OSPS is Oral Sodium Phosphate Solution
MoviPrep's responder rate was not significantly higher than OSPS's responder rate.

16 HOW SUPPLIED/STORAGE AND HANDLING

MoviPrep® is supplied in powdered form. MoviPrep is administered as an oral solution after reconstitution.

NDC 54868-5890-0, MoviPrep, single use carton.

Each carton contains a disposable container for reconstitution of MoviPrep® and an inner carton containing 4 pouches (2 of pouch A and 2 of pouch B).

Rx only

STORAGE
Store carton/container at 25°C (77°F); excursions permitted to 15-30°C (59-86°F). When reconstituted, store upright and keep solution refrigerated. Use within 24 hours.

17 PATIENT COUNSELING INFORMATION

Important Precautions Regarding MOVIPREP

MoviPrep produces a watery stool which cleanses the colon before colonoscopy. It is recommended that patients receiving MoviPrep be advised to adequately hydrate before, during, and after the use of MoviPrep. Patients may have clear soup and/or plain yogurt for dinner, finishing the evening meal at least one hour prior to the start of MoviPrep treatment. No solid food should be taken from the start of MoviPrep treatment until after the colonoscopy.

What Patients Should Know About Adverse Reactions

The first bowel movement may occur approximately 1 hour after the start of MoviPrep administration. Abdominal bloating and distention may occur before the first bowel movement. If severe abdominal discomfort or distention occurs, stop drinking temporarily or drink each portion at longer intervals until these symptoms disappear.

Manufactured by:
Norgine B.V.
Hogehilweg 7
1101 CA Amsterdam Zuidoost
Netherlands

For:
Salix Pharmaceuticals, Inc.
Morrisville, NC 27560

© 2006 Salix Pharmaceuticals, Inc.
VENART xxx-x/June 09

Product protected by U.S. Patent No. 7169381 and other pending applications

PRINCIPAL DISPLAY PANEL

MoviPrep®
(PEG-3350, Sodium Sulfate, Sodium Chloride, Potassium Chloride, Sodium Ascorbate and Ascorbic Acid for Oral Solution)

Phenylketonurics:
contains phenylalanine – a maximum of 2.33 mg per course of treatment.

This carton contains
One container for reconstitution of MoviPrep®